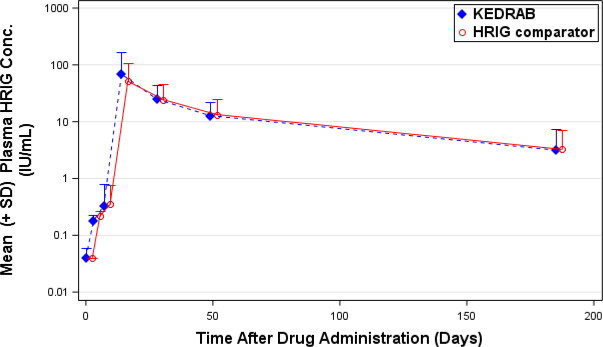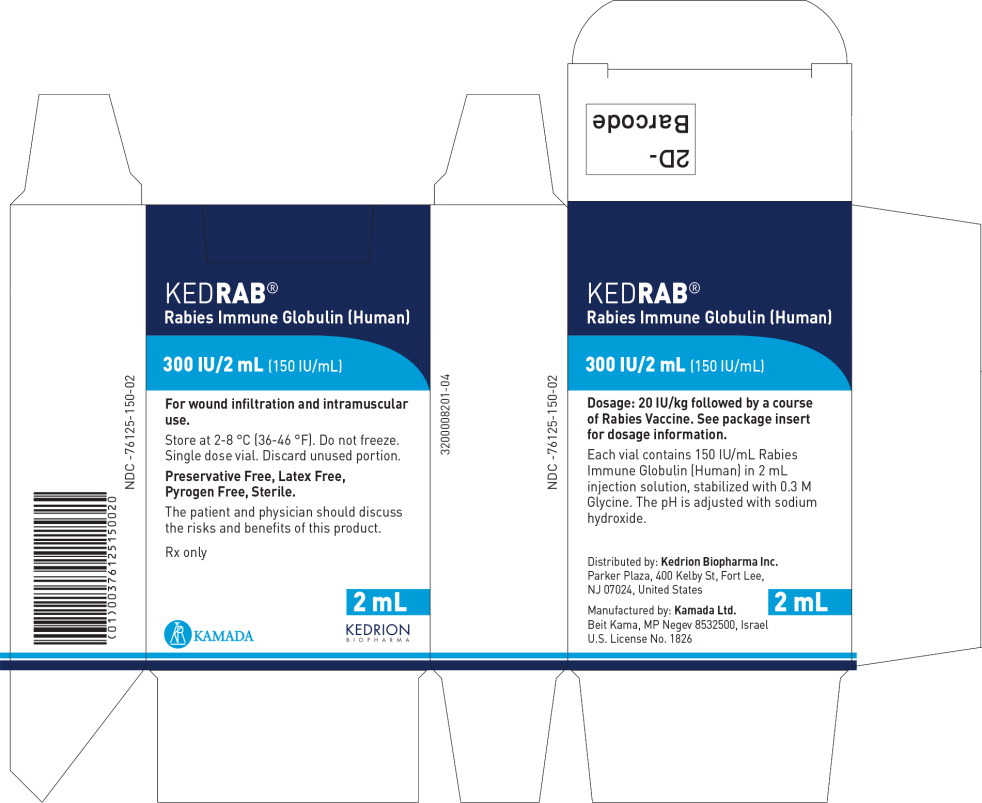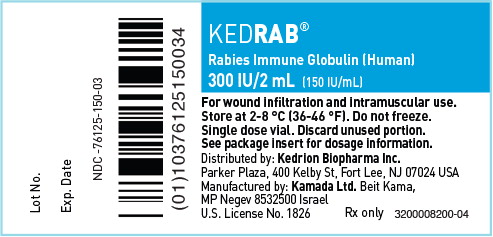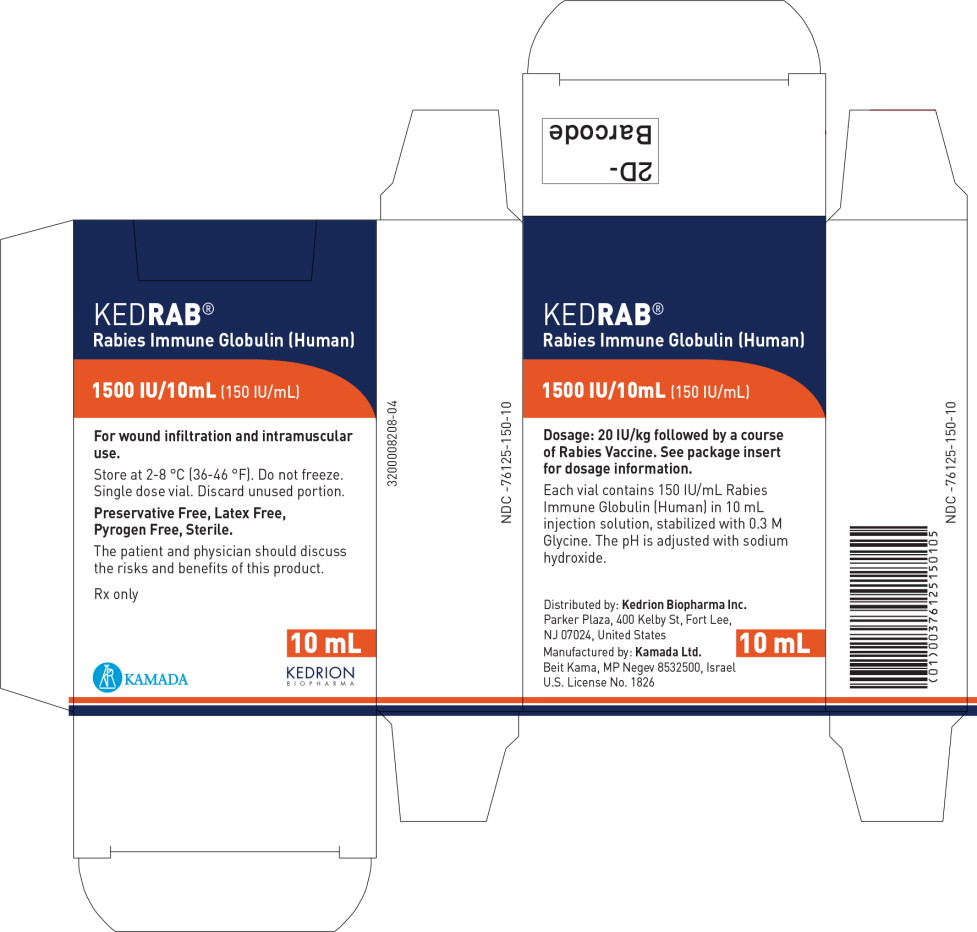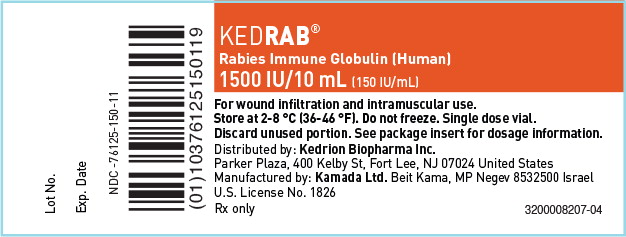 DRUG LABEL: KEDRAB
NDC: 76125-150 | Form: INJECTION, SOLUTION
Manufacturer: Kedrion Biopharma Inc.
Category: other | Type: PLASMA DERIVATIVE
Date: 20240221

ACTIVE INGREDIENTS: HUMAN RABIES VIRUS IMMUNE GLOBULIN 150 [iU]/1 mL
INACTIVE INGREDIENTS: GLYCINE; WATER

HIGHLIGHTS OF PRESCRIBING INFORMATION

These highlights do not include all the information needed to use KEDRAB safely and effectively. See full prescribing information for KEDRAB.
KEDRAB®Rabies Immune Globulin (Human) solution for wound infiltration and intramuscular injection
Initial U.S. Approval: 2017

RECENT MAJOR CHANGES

Indications and Usage (1) | 05/2021
Dosage and Administration (2) | 05/2021

1 INDICATIONS AND USAGE

KEDRAB is a human rabies immune globulin (HRIG) indicated for passive, transient post-exposure prophylaxis of rabies infection to persons of all ages when given immediately after contact with a rabid or possibly rabid animal. KEDRAB should be administered concurrently with a full course of rabies vaccine. (1)

2 DOSAGE AND ADMINISTRATION

For wound infiltration and intramuscular use. (2)

Post-exposure prophylaxis: single dose of KEDRAB with a full course of rabies vaccine | 20 IU/kg body weight KEDRAB Do not exceed recommended dose. Do not repeat KEDRAB doses once vaccine treatment is initiated. | - Administer as soon as possible after exposure - Infiltrate area around wound with full dose - Inject any remaining KEDRAB intramuscularly, at a site distant from the site of rabies vaccine administration

3 DOSAGE FORMS AND STRENGTHS

Single-dose vials containing 2 mL or 10 mL ready-to-use solution with a potency of 150 IU/mL.(3)

4 CONTRAINDICATIONS

None. (4)

5 WARNINGS AND PRECAUTIONS

- Do not give KEDRAB to persons who have completed rabies pre- or post-exposure prophylaxis because it can interfere with the anamnestic response to the rabies vaccine. (5.1)
- Hypersensitivity reactions, including anaphylaxis, may occur with KEDRAB. IgA deficient patients with antibodies against IgA are at greater risk. Have epinephrine available immediately to treat any acute severe hypersensitivity reactions. (5.2)
- Interference with live attenuated virus vaccines. (5.5, 7)
- KEDRAB is made from human plasma, and may carry a risk of transmitting infectious agents, e.g., viruses, the variant Creutzfeldt-Jakob disease (vCJD) agent, and theoretically, the Creutzfeldt-Jakob disease (CJD) agent. (5.7)

6 ADVERSE REACTIONS

The most common adverse reactions (>5%) observed in adult subjects were injection site pain, headache, muscle pain, joint pain, dizziness, and fatigue.

The most common adverse reactions (>5%) observed in pediatric patients were injection site pain, headache, pyrexia, plain in extremity, bruising, fatigue, and vomiting. (6.1)

To report SUSPECTED ADVERSE REACTIONS, contact Kedrion Biopharma Inc. at 1-855-353-7466 or FDA at 1-800-FDA-1088 or www.fda.gov/medwatch.

7 DRUG INTERACTIONS

Do not administer KEDRAB in the same syringe, or into the same anatomical site, as the rabies vaccine. (2, 7)

FULL PRESCRIBING INFORMATION

1 INDICATIONS AND USAGE

KEDRAB is a human rabies immune globulin (HRIG) indicated for passive, transient post-exposure prophylaxis (PEP) of rabies infection to persons of all ages when given immediately after contact with a rabid or possibly rabid animal. KEDRAB should be administered concurrently with a full course of rabies vaccine.

2 DOSAGE AND ADMINISTRATION

For wound infiltration and intramuscular use.

2.1 Dosage

Post-exposure prophylaxis consists of a single 20 IU/kg body weight dose of KEDRAB and a full course of rabies vaccine (See Table 1).

Table 1: Rabies Post-exposure Prophylaxis Schedule*
Vaccination Status | Intervention | Regimen†
Not previously vaccinated | Wound Cleansing | - Cleanse all wounds immediately and thoroughly with soap and water. - Irrigate the wounds with a viricidal agent such as a povidone-iodine solution, if available.
Not previously vaccinated | KEDRAB®20 IU/kg body weight | - Administer KEDRAB as soon as possible after exposure, preferably at the time of the first rabies vaccine dose. However, should a delay occur, administer KEDRAB at any time up to and including seven days after the first dose of rabies vaccine. - If there is a delay, initiate post-exposure prophylaxis at any time after exposure. - Infiltrate the area around and into the wound(s), if anatomically feasible, with the full dose of KEDRAB. - Inject the remainder, if any, intramuscularly at an anatomical site distant from the site of rabies vaccine administration. - Do not exceed the recommended dose of KEDRAB because this can partially suppress active production of rabies virus antibodies. [see Drug Interactions (7)] - Do not administer additional doses of KEDRAB, even if the antibody response to vaccination is delayed. (7) - Use separate syringes, needles, and anatomical injection sites for KEDRAB and for rabies vaccine.
Not previously vaccinated | Rabies Vaccine | - Administer rabies vaccine on Day 0 and on subsequent vaccine administration daysǂ at an anatomical site that is distant from the KEDRAB administration site(s). - Complete a rabies vaccination series
Previously vaccinated§ | Wound cleansing | - Cleanse all wounds immediately and thoroughly with soap and water. - Irrigate the wounds with a viricidal agent such as povidone-iodine solution if available.
Previously vaccinated§ | KEDRAB® | - Do not administer KEDRAB. [see Warnings and Precautions (5.1)]
Previously vaccinated§ | Rabies Vaccine | - Administer rabies vaccine on Day 0.ǂ - Complete a rabies vaccination series for previously vaccinated persons.†
Other Considerations | Tetanus prophylaxis and/or antibiotics | - Provide treatment if medically indicated
* Adapted from reference 1.
†These regimens are applicable for all age groups, including children.
ǂ Day 0 is the day the first dose of vaccine is administered. Refer to vaccine manufacturer's instructions or to the recommendations of the Advisory Committee on Immunization Practices (ACIP)^1,2for appropriate rabies vaccine formulations, schedules, and dosages.
§Any person with a history of rabies vaccination and a documented history of antibody response to the prior vaccination.

2.2 Administration

Infiltrate as much of the KEDRAB dose as possible into and around any detectable bite wounds if infiltration at the bite site is feasible. Administer any remaining KEDRAB intramuscularly into anatomical site(s) distant from the site of the rabies vaccine.

- When the bite site is unknown or indeterminate (undetectable) or if infiltration is difficult at the bite site (e.g., lips, fingers, knee), administer the full KEDRAB dose by the intramuscular route at a site distant from the site of rabies vaccination.
- If a large intramuscular volume is required (>2 mL for children or >5 mL for adults), administer the total volume in divided doses at different sites.
- Do not mix KEDRAB with the rabies vaccine or administer in the same syringe with the rabies vaccine.
- Discard unused portion of the product in the vial.

Parenteral drug products should be inspected visually for particulate matter and discoloration prior to administration. Do not use if either of these conditions exists, and contact Kedrion Biopharma Inc. at 1-855-353-7466. Do not discard the vial.

3 DOSAGE FORMS AND STRENGTHS

KEDRAB is supplied in single-dose vials containing 2 mL or 10 mL of ready-to-use solution with a nominal potency of 150 IU/mL (Note that more than one vial may be required for a single patient treatment).

- The 2 mL vial contains a total of 300 IU, which is sufficient for a child weighing 15 kg (33 lb)
- The 10 mL vial contains a total of 1500 IU, which is sufficient for an adult weighing 75 kg (165 lb)

The final product is assayed with human rabies immunoglobulin reference standard that is calibrated against the WHO International Standard.

4 CONTRAINDICATIONS

None.

5 WARNINGS AND PRECAUTIONS

5.1 Previous Rabies Vaccination

Patients who can document previous complete rabies pre-exposure prophylaxis or complete post-exposure prophylaxis should only receive a booster rabies vaccine without KEDRAB because KEDRAB may interfere with the anamnestic response to the vaccine (ACIP)^1.

5.2 Hypersensitivity Reactions

Hypersensitivity reactions, including anaphylaxis, may occur with KEDRAB. History of prior systemic allergic reactions to human immunoglobulin preparations places patients at greater risk. Have epinephrine available for treatment of acute allergic symptoms. Patients with isolated immunoglobulin A (IgA) deficiency may develop severe hypersensitivity reactions to KEDRAB or, subsequently, to the administration of blood products that contain IgA.

5.5 Live Attenuated Virus Vaccines

KEDRAB administration may interfere with the development of an immune response to live attenuated virus vaccines. If feasible, delay immunization with measles vaccine for 4 months, and other live attenuated virus vaccines for 3 months, after KEDRAB administration.

5.6 Interference with Serologic Testing

- A transient rise of the various passively transferred antibodies in the patient's blood may result in misleading positive results of serologic tests after KEDRAB administration.
- Passive transmission of antibodies to erythrocyte antigens, e.g., A, B, and D, may interfere with serologic tests for red cell antibodies such as the antiglobulin test (Coombs' test).

5.7 Transmissible Infectious Agents

Because KEDRAB is made from human plasma donors hyper-immunized with rabies vaccine, it may carry a risk of transmitting infectious agents, e.g., viruses, the variant Creutzfeldt-Jakob disease (vCJD) agent and, theoretically, the Creutzfeldt-Jakob disease (CJD) agent. All infections suspected by a physician possibly to have been transmitted by this product should be reported by the physician or other healthcare provider to Kedrion Biopharma Inc. at 1-855-353-7466.

6 ADVERSE REACTIONS

The most common adverse reactions (>5%) observed in adult subjects were injection site pain, headache, muscle pain, joint pain, dizziness, and fatigue.

The most common adverse reactions (>5%) observed in pediatric patients were injection site pain, headache, pyrexia, plain in extremity, bruising, fatigue and vomiting.

6.1 Clinical Trials Experience

Because clinical trials are conducted under widely varying conditions, adverse reaction rates observed in clinical trials of a drug cannot be directly compared to rates of adverse reactions in clinical trials of another drug and may not reflect the rates observed in clinical practice.

KEDRAB was evaluated in three single-center, controlled clinical trials in adults. Subjects in these clinical studies of KEDRAB were healthy adults, primarily white, and ranged in age from 18 to 72 years. A total of 160 adult subjects were treated in these three studies, including 91 subjects who received single intramuscular doses of KEDRAB (20 IU/kg) with or without rabies vaccine.

Table 2summarizes adverse reactions occurring in >3% of adult subjects in the clinical trials of KEDRAB. (Table 2).

Table 2: Adverse Reactions Occurring in >3% of Subjects in All Combined Studies in Adults
 | All KEDRAB (N=91) | All Comparator HRIG (N=84) | Saline Placebo+Vaccine (N=8)
Injection site pain | 30 (33%) | 26 (31%) | 2 (25%)
Headache | 14 (15%) | 11 (13%) | 3 (38%)
Muscle pain | 8 (9%) | 6 (7%) | 0 (0%)
Joint Pain | 5 (6%) | 0 (0%) | 1 (13%)
Dizziness | 5 (6%) | 3 (4%) | 0 (0%)
Fatigue | 5 (6%) | 2 (2%) | 0 (0%)
Abdominal pain | 4 (4%) | 1 (1%) | 0 (0%)
Blood in urine (Hematuria) | 4 (4%) | 2 (2%) | 0 (0%)
Nausea | 4 (4%) | 3 (4%) | 0 (0%)
Feeling faint | 4 (4%) | 1 (1%) | 0 (0%)
Data are presented as number of subjects (% of subjects).

Less frequent adverse reactions (≤3%) in adult subjects were diarrhea, vomiting, decreased appetite, musculoskeletal stiffness, malaise, weakness (asthenia), fainting (syncope), itching (pruritis), tingling sensation (paresthesia), rash, sunburn and elevation in liver function.

KEDRAB was also evaluated in a two-center, open-label clinical trial in 30 pediatric patients exposed or possibly exposed to rabies virus. They ranged in age from 0.5 to 14.9 years. Study treatment included a single dose of KEDRAB (20 IU/kg) and active rabies vaccine on Days 0, 3, 7 and 14 administered as per ACIP^1recommendations for rabies post-exposure prophylaxis.

Twelve pediatric patients (40%) experienced adverse reactions within 14 days of receipt of KEDRAB and first dose of rabies vaccine. There were no serious adverse reactions. Table 3summarizes the adverse reactions that occurred in >5% of patients in the pediatric clinical trial within 14 days of receipt of KEDRAB and the first dose of the rabies vaccine.

Table 3: Adverse Reactions Occurring in >5% of Pediatric Patients within 14 Days of Post-exposure Prophylaxis with KEDRAB and Active Rabies Vaccine
 | KEDRAB + Rabies Vaccine N = 30
Injection site pain | 8 (27%)
Headache | 4 (13%)
Fever (Pyrexia) | 4 (13%)
Pain in extremity | 3 (10%)
Bruising (hematoma) | 2 (7%)
Fatigue | 2 (7%)
Vomiting | 2 (7%)
Data are presented as number of patients (% of patients).

Less common adverse reactions (≤5%) in pediatric patients were injection site redness (erythema), injection site swelling (edema), muscle pain, oral pain, and wound complication.

Insomnia was reported as a less common adverse reactions (<5%) in pediatric patients occurring after 14 days of administration.

7 DRUG INTERACTIONS

- Patients who can document previous complete rabies pre-exposure prophylaxis or complete post-exposure prophylaxis and have a confirmed adequate rabies antibody titer should receive only a booster rabies vaccine (without KEDRAB) because KEDRAB may interfere with the anamnestic response to the vaccine (ACIP)^1.
- KEDRAB can interfere with the immune response to the rabies vaccine. For this reason, do not exceed the recommended KEDRAB dose or give additional (repeat) doses of KEDRAB once rabies vaccination has been initiated.
- KEDRAB can inactivate the rabies vaccine. For this reason, do not administer KEDRAB in the same syringe as the rabies vaccine or near the anatomical site of administration of the rabies vaccine.
- KEDRAB contains other antibodies that may interfere with the response to live vaccines such as measles, mumps, polio or rubella. Avoid immunization with live virus vaccines within 3 months after KEDRAB administration, or in the case of measles vaccine, within 4 months after KEDRAB administration.

8 USE IN SPECIFIC POPULATIONS

8.1 Pregnancy

Risk Summary

KEDRAB has not been studied in pregnant women. Therefore, the risk of major birth defects and miscarriage in pregnant women who are exposed to KEDRAB is unknown. Animal developmental or reproduction toxicity studies have not been conducted with KEDRAB. It is not known whether KEDRAB can cause harm to the fetus when administered to a pregnant woman or whether KEDRAB can affect reproductive capacity. In the U.S. general population, the estimated background of major birth defects occurs in 2-4% of the general population and miscarriage occurs in 15-20% of clinically recognized pregnancies.

8.2 Lactation

Risk Summary

There is no information regarding the presence of KEDRAB in human milk, the effects on the breastfed infant, or the effects on milk production. The developmental and health benefits of breastfeeding should be considered along with the mother's clinical need for KEDRAB and any potential adverse effects on the breastfed infant from KEDRAB or from the underlying maternal condition.

8.4 Pediatric Use

Safety and effectiveness have been established in children. In a pediatric study of 30 patients ranging in age from 0.5 to 14.9 years, KEDRAB presented no serious adverse reactions through day 84. Of the 30 patients, 28 (93.3%) achieved a Day-14 RVNA titer ≥0.5 IU/mL, the WHO recommended level. None of the patients who were followed until the end of the study (28/30 patients) developed rabies infection through day 84. [see Clinical Trials (14)]

Adverse reactions that occurred in ≥3.3% of patients within the first 14 days of KEDRAB and the first rabies vaccination administration are listed in Section 6.1.

The clinical trial conducted in the pediatric population is described in Section 14.

Additional evidence to support the use of KEDRAB in children comes from Real World Evidence. Based on claims data, 172 U.S. children (≤17 years) were treated with KEDRAB between 2018-2020. Based on Center for Disease Control data, no children in the U.S. treated with post-exposure prophylaxis have been reported to have had rabies between 2018-April 2021.

8.5 Geriatric Use

Clinical studies of KEDRAB did not include sufficient numbers of subjects aged 65 years and over to determine whether they respond differently from younger subjects. Clinical experience with HRIG products has not identified differences in effectiveness between elderly and younger patients (ACIP)^1.

11 DESCRIPTION

KEDRAB is a sterile, non-pyrogenic aqueous solution of anti-rabies immunoglobulin (≥95% protein as IgG). The product is stabilized with 0.3 M glycine and has a pH of 5.5 ± 0.5. It does not contain preservatives and the vial stopper is not made with natural rubber latex. KEDRAB is a clear to opalescent liquid.

KEDRAB is prepared from human plasma from donors hyper-immunized with rabies vaccine. Individual plasma units are tested using FDA-licensed serologic assays for hepatitis B surface antigen (HBsAg) and for antibodies to hepatitis C virus (HCV) and human immunodeficiency virus types 1 and 2 (HIV-1/2), as well as by FDA-licensed Nucleic Acid Testing (NAT) for hepatitis B virus (HBV), HCV and HIV-1. Each plasma unit must be non-reactive (negative) in all tests. Plasma is also tested by in-process NAT procedures for HAV and parvovirus B19. Each plasma unit must be non-reactive to HAV, while the limit in the manufacturing pool is set not to exceed 10^4IU per mL for parvovirus B19. The KEDRAB manufacturing process includes three validated and effective viral elimination steps:

- Solvent/detergent (S/D) treatment - inactivates enveloped viral agents
- Heat inactivation (pasteurization) - inactivates both enveloped and non-enveloped viruses
- Nanofiltration (NF) - physically removes viruses

The effectiveness of the S/D treatment, pasteurization and nanofiltration procedures for reducing viral content has been assessed using a series of viruses with a range of physico-chemical characteristics. The results of the viral challenge studies are summarized in Table 4.

Table 4: Log10Virus Reduction during Manufacture of KEDRAB
Process Step | Enveloped Viruses |  |  |  | Non-enveloped Viruses
Process Step | HIV-1 | BVDV | PRV | WNV | EMCV | PPV
S/D treatment | >4.99 | >5.70 | >4.38 | >5.46 | Not tested | Not tested
Heat treatment | >6.21 | >5.67 | Not tested | >6.33 | 3.30 | Not tested
Nanofiltration | Not tested | Not tested | >6.58 | Not tested | >7.66 | 3.41
Global Log 10 Reduction Factor | >11.20 | >11.37 | >10.96 | >11.79 | >10.96 | 3.41
Abbreviations: BVDV: bovine viral diarrhea virus; EMCV: encephalomyocarditis virus; HIV-1: human immunodeficiency virus 1; HRIG: human rabies immune globulin; PPV: Porcine parvovirus; PRV: Pseudorabies virus; S/D: solvent/detergent; WNV: West Nile Virus.

12 CLINICAL PHARMACOLOGY

12.1 Mechanism of Action

Rabies is a zoonotic disease caused by RNA viruses in the family Rhabdoviridae, genus Lyssavirus. Virus is typically present in the saliva of rabid mammals and is transmitted primarily through a bite. KEDRAB is infiltrated into the inoculation site(s) in previously unvaccinated persons, to provide immediate passive rabies virus neutralizing antibody protection until the patient's immune system responds to vaccination by actively producing antibodies.

12.2 Pharmacodynamics

A protective threshold for rabies virus neutralizing activity (RVNA) has never been established. However, the WHO has generally accepted a RVNA of at least 0.5 IU/mL measured 14 days after initiation of post-exposure prophylaxis as protective.

12.3 Pharmacokinetics

A randomized, single-dose, two-period, two-treatment, two-sequence, double-blind, crossover study assessed the pharmacokinetics of KEDRAB. Twenty-six healthy volunteer subjects were randomized to receive a single IM injection of 20 IU/kg HRIG on two separate occasions (KEDRAB or Comparator HRIG). Subjects received the second treatment (A or B) following the 42-day test period and a 21-day washout period. Single dose IM injection of KEDRAB resulted in maximum plasma RVNA levels of 0.25 IU/mL. The median Tmaxwas 7 days (range: 3-14 days). The elimination half-life was approximately 17.9 days. A statistical analysis of the pharmacokinetic parameters showed that KEDRAB was not bioequivalent to the Comparator HRIG (Table 5).

Table 5: Statistical Analysis of Rabies Virus Neutralizing Antibody Pharmacokinetic Parameters - Crossover Study of KEDRAB
Parameter | Units | Geometric LS Mean Values |  | Test/Reference (%) | 90% Confidence Interval (%)
Parameter | Units | KEDRAB | Comparator HRIG | Test/Reference (%) | 90% Confidence Interval (%)
Cmax | IU/mL | 0.24 | 0.30 | 81.71 | 75.34-88.62
AUC0-last | Day*IU/mL | 5.08 | 6.17 | 82.35 | 77.39-87.63
AUC0-inf | Day*IU/mL | 6.64 | 7.86 | 84.44 | 78.63-90.68
Abbreviations: AUC: area under the concentration-time curve; Cmax: maximum concentration; inf: infinity; IU: international units; mL: milliliter; PK: Pharmacokinetic; RVNA: rabies virus neutralizing antibody

A plot of plasma rabies virus neutralizing antibody titer concentration versus time (Figure 1) demonstrated that, in both treatment groups, plasma rabies virus neutralizing antibody concentrations declined in a biphasic manner after the absorption phase was complete.

Figure 1: Plasma HRIG Concentrations [Mean (±SD)] at Scheduled PK Sampling Days (Semi-log Scale), Phase 2/3 Study, Pharmacokinetic Analysis

Additionally, a prospective, randomized, double-blind, non-inferiority, study evaluated the pharmacokinetics, safety, and effectiveness of simulated post-exposure prophylaxis with KEDRAB with co-administration of active rabies vaccine in 118 healthy subjects. Subjects were randomized into two treatment groups (59 per treatment group) to receive intramuscular KEDRAB or comparator HRIG at a dose of 20 IU/kg on Day 0, and rabies vaccine on Days 0, 3, 7, 14 and 28. The peak plasma RVNA was 71.9 IU/mL and 53.9 IU/mL for KEDRAB and comparator HRIG respectively. For both treatment groups, the median Tmaxwas 14 days (range: 14-49 days). The half-lives were 48.6 hours and 52.7 hours for KEDRAB and comparator HRIG respectively.

Bioequivalent assessment showed that KEDRAB was not bioequivalent to the comparator HRIG when co-administered with a five-dose rabies vaccine regimen (Table 6). Furthermore, the RVNA on Day 3 was lower in the KEDRAB with rabies vaccine group relative to the comparator HRIG with vaccine group (0.188+0.051 vs 0.229+0.054, P=0.0005). However, these pharmacokinetic differences are not expected to affect clinical outcomes.

Table 6: Pharmacokinetic Comparison of Rabies Virus Neutralizing Antibody between KEDRAB and a Comparator HRIG Administered with Rabies Vaccine
Parameter | Units | Geometric LS Mean Values |  | Test/Reference (%) | 90% Confidence Interval (%)
Parameter | Units | KEDRAB (Test) | Comparator HRIG (Reference) | Test/Reference (%) | 90% Confidence Interval (%)
Cmax | IU/mL | 44.87 | 36.02 | 124.59 | 90.62-171.28
AUC0-last | Day*IU/mL | 1741.40 | 1686.03 | 103.28 | 79.03-134.98
AUC0-inf | Day*IU/mL | 2045.87 | 1916.90 | 106.73 | 80.48-141.54
Abbreviations: AUC: area under the concentration-time curve; Cmax: maximum concentration; inf: infinity; IU: international units; mL: milliliter; RVNA: rabies virus neutralizing antibody

Please see Clinical Studies (14) section for clinical efficacy.

13 NONCLINICAL TOXICOLOGY

13.2 Animal Toxicology and/or Pharmacology

Intramuscular administration of a single dose of KEDRAB to rats at 60 and 120 IU/kg (3-fold and 6-fold higher than the recommended human dose of 20 IU/kg) did not result in any signs of toxicity.

14 CLINICAL STUDIES

The efficacy of KEDRAB administered concurrently with rabies vaccine was studied in a single-center, randomized, comparator HRIG-controlled clinical study in adults. Study subjects were healthy adults 18 to 72 years of age who were without significant acute or chronic illness. A total of 118 subjects (59 per treatment group) received intramuscular KEDRAB or comparator HRIG at a dose of 20 IU/kg on Day 0, and rabies vaccine on Days 0, 3, 7, 14 and 28. The mean age of study subjects was 45 years; subjects were, predominantly white (93%), and 64% were women. The efficacy variable was RVNA, as assessed by Rapid Fluorescent Focus Inhibition Test (RFFIT), on Day 14. Efficacy analyses were performed on the As-Treated Population, which comprised the 116 study subjects who received KEDRAB or comparator HRIG and at least 3 of the 5 doses of rabies vaccine before Day 14.

Efficacy, considered when RVNA titer is 0.5 IU/mL or higher on Day 14 (as established by the WHO), was met by 56/57 subjects (98.2%) in the KEDRAB group and 59/59 subjects in the comparator HRIG group (Table 7). The lower limit of the 90% CI was greater than the pre-specified non-inferiority margin of -10%; thus, KEDRAB was non-inferior to comparator HRIG.

Table 7: Subjects with Geometric Mean RVNA ≥0.5 IU/mL on Day 14 (As-Treated Population)
 | KEDRAB with Rabies Vaccine (N=57) | Comparator HRIG with Rabies Vaccine (N=59)
Rabies virus neutralizing antibody titer ≥0.5 IU/mL, n (%) | 56 (98.2) | 59 (100)
Exact 95% CI for proportion (%) | (90.6, 100) | (93.9, 100)
Difference (Pa-Pb)a(%) | -1.8
Exact 90% CI for differenceb(%) | (-8.1, 3.0)
a'Pa' and 'Pb' are the proportion of participants with IgG antibody titer ≥0.5 IU/mL on Day 14 in Groups A and B, respectively. Group A = KEDRAB +Rabies Vaccine, Group B = Control HyperRAB®+Rabies Vaccine.
bbased on Farrington-Manning score statistic.
Abbreviations: CI: confidence interval; HRIG: human rabies immune globulin; IU: international units; mL: milliliter

Additional efficacy analyses in adult subjects included pharmacokinetics [see Clinical Pharmacology (12) ].

KEDRAB was also evaluated in a two-center, open-label clinical trial in 30 pediatric patients exposed or possibly exposed to rabies virus for whom post-exposure prophylaxis was indicated. The patients were treated with KEDRAB at a dose of 20 IU/kg on Day 0 and active rabies vaccine on Days 0, 3, 7, and 14 as per ACIP^1recommendations for rabies post-exposure prophylaxis. The patients ranged in age from 0.5 to 14.9 years, 46.7% were females, 6.7% were Asian, 23.3% were Black and 70% were White, 10% were Latino. The efficacy variables were RVNA as assessed by RFFIT on Day 14 and occurrence of rabies disease through Day 84 after administration of KEDRAB. Efficacy analyses were performed on the As-Treated Population, which comprised all 30 study patients.

In the As-Treated Population, the geometric mean (SD) Day-14 RVNA titer was 18.89 (31.61) IU/mL and the median Day-14 RVNA titer was 8.81 (range 0.21 – 153.62) IU/mL. Of the 30 treated pediatric patients, 28 patients (93.3%) had a Day-14 RVNA titer ≥ 0.5 IU/mL, the WHO recommended level. None of the 28/30 patients who were followed for the duration of the study developed rabies infection through day 84.

15 REFERENCES

1. Centers for Disease Control and Prevention. Human rabies prevention—United States, 2008: Recommendations of the Advisory Committee on Immunization Practices (ACIP). MMWR 2008;57 (No. RR-3).
2. Use of a Reduced (4-Dose) Vaccine schedule for postexposure prophylaxis to prevent human rabies: Recommendations of the Advisory Committee on Immunization Practices. MMWR 2010;59 (No. RR-2).
3. WHO 2018, Expert Consultation on Rabies. Third Report. Geneva: WHO Press. Technical Report Series (No. 1012).

16 HOW SUPPLIED/STORAGE AND HANDLING

- Each package of KEDRAB contains a single-dose vial containing 2 mL or 10 mL of ready-to-use solution with a potency of 150 IU/mL (Note that more than one vial may be required for a single patient treatment).
- The 2-mL vial contains a total of 300 IU which is sufficient for a child weighing 15 kg (33 lb). (NDC 76125-150-02). The 10-mL vial contains a total of 1500 IU which is sufficient for an adult weighing 75 kg (165 lb). (NDC 76125-150-10)
- Keep vial in package until use.
- Store KEDRAB at 2-8 °C (36-46 °F). DO NOT FREEZE.
- KEDRAB may be stored at room temperatures not exceeding 25 °C (77 °F) for up to one month.
- Use within one month after removal from refrigeration. Do not return to refrigeration.
- Do not use after the expiration date printed on the label.

17 PATIENT COUNSELING INFORMATION

- Inform patients that KEDRAB is made from human plasma and may contain infectious agents that can cause disease (e.g., viruses and, theoretically, the CJD agent). Symptoms of a possible viral infection include headache, fever, nausea, vomiting, weakness, malaise, diarrhea, or, in the case of hepatitis, jaundice. Patients should contact their healthcare provider if any of these symptoms develop. [see Warnings and Precautions (5.7) ].
- Remind patients that it is necessary to complete the rabies vaccine series.

Distributed by:
Kedrion Biopharma Inc.
Parker Plaza, 400 Kelby St.
Fort Lee, NJ 07024
United States
Manufactured by:
Kamada Ltd.
Beit Kama
MP Negev 8532500
Israel
US License No. 1826

Principal Display Panel – 2mL Carton Label

NDC-76125-150-02

KED RAB
Rabies Immune Globulin (Human)

300 IU/2mL (150 IU/mL)

For wound infiltration and intramuscular
use.

Store at 2-8 °C (36-46 °F). Do not freeze.
Single dose vial. Discard unused portion.

Preservative Free, Latex Free,
Pyrogen Free, Sterile .

The patient and physician should discuss
the risks and benefits of this product.

Rx only

2 mL

KAMADA

KEDRION
BIOPHARMA

Principal Display Panel – 2mL Vial Label

NDC-76125-150-03

KED RAB Rabies Immune Globulin (Human)

300 IU/2mL (150 IU/mL)

For wound infiltration and intramuscular use.
Store at 2-8 °C (36-46 °F). Do not freeze.

Single dose vial. Discard unused portion.

See package insert for dosage information.
Distributed by: Kedrion Biopharma Inc.
Parker Plaza, 400 Kelby St, Fort Lee, NJ 07024 USA
Manufactured by: Kamada Ltd. Beit Kama,

MP Negev 8532500 Israel
U.S. License No. 1826 Rx only

Principal Display Panel – 10mL Carton Label

NDC-76125-150-10

KED RAB
Rabies Immune Globulin (Human)

1500 IU/10mL (150 IU/mL)

For wound infiltration and intramuscular
use.

Store at 2-8 °C (36-46 °F). Do not freeze.
Single dose vial. Discard unused portion.

Preservative Free, Latex Free,
Pyrogen Free, Sterile .

The patient and physician should discuss
the risks and benefits of this product.

Rx only

10 mL

KAMADA

KEDRION
BIOPHARMA

Principal Display Panel – 10mL Vial Label

NDC-76125-150-11

KED RAB Rabies Immune Globulin (Human)

1500 IU/10mL (150 IU/mL)

For wound infiltration and intramuscular use.
Store at 2-8 °C (36-46 °F). Do not freeze. Single dose vial.

Discard unused portion. See package insert for dosage information.
Distributed by: Kedrion Biopharma Inc.
Parker Plaza, 400 Kelby St, Fort Lee, NJ 07024 United States
Manufactured by: Kamada Ltd.Beit Kama MP Negev 8532500 Israel
U.S. License No. 1826 Rx only